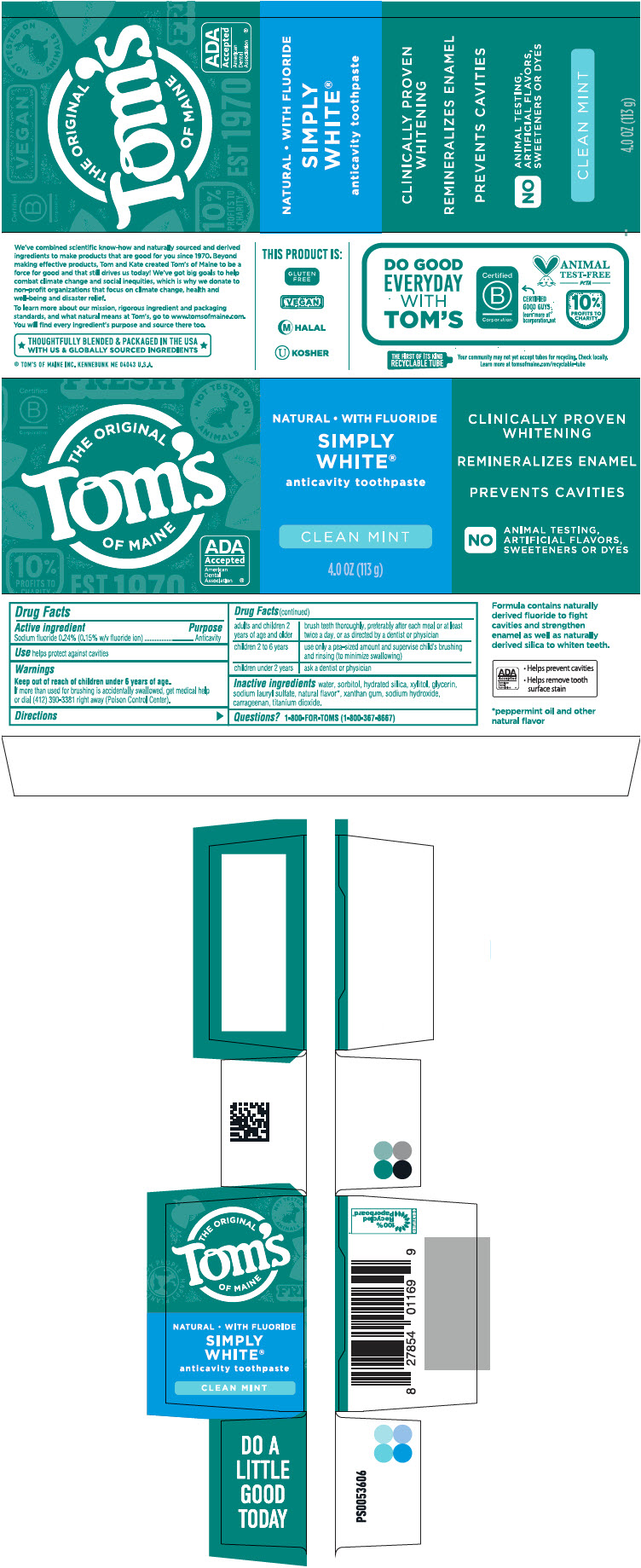 DRUG LABEL: Simply White
NDC: 51009-248 | Form: PASTE, DENTIFRICE
Manufacturer: Tom's of Maine, Inc.
Category: otc | Type: HUMAN OTC DRUG LABEL
Date: 20251113

ACTIVE INGREDIENTS: SODIUM FLUORIDE 0.00243 g/1 g
INACTIVE INGREDIENTS: SORBITOL; WATER; HYDRATED SILICA; GLYCERIN; XYLITOL; SODIUM LAURYL SULFATE; XANTHAN GUM; CARRAGEENAN; TITANIUM DIOXIDE; SODIUM HYDROXIDE

Tom's
OF MAINE
SIMPLY WHITE®
fluoride toothpaste
clean mint

Drug Facts

Active ingredient

Sodium fluoride 0.24% (0.15% w/v fluoride ion)

Purpose

Anticavity

Use

helps protect against cavities

Warnings

Keep out of reach of children under 6 years of age.

If more than used for brushing is accidentally swallowed, get medical help or dial (412) 390-3381 right away (Poison Control Center).

Directions

adults and children 2 years of age and older | brush teeth thoroughly, preferably after each meal or at least twice a day, or as directed by a dentist or physician
children 2 to 6 years | use only a pea-sized amount and supervise child's brushing and rinsing (to minimize swallowing)
children under 2 years | ask a dentist or physician

Inactive ingredients

water, sorbitol, hydrated silica, xylitol, glycerin, sodium lauryl sulfate, natural flavor [peppermint oil and other natural flavor] , xanthan gum, sodium hydroxide, carrageenan, titanium dioxide.

Questions?

1-800-FOR-TOMS (1-800-367-8667)

PRINCIPAL DISPLAY PANEL - 113 g Tube Carton

THE ORIGINAL
Tom's
OF MAINE

ADA
Accepted
American
Dental
Association ®

NATURAL • WITH FLUORIDE

SIMPLY
WHITE®

anticavity toothpaste

CLEAN MINT

4.0 OZ (113 g)

CLINICALLY PROVEN
WHITENING

REMINERALIZES ENAMEL

PREVENTS CAVITIES

NO
ANIMAL TESTING,
ARTIFICIAL FLAVORS,
SWEETENERS OR DYES